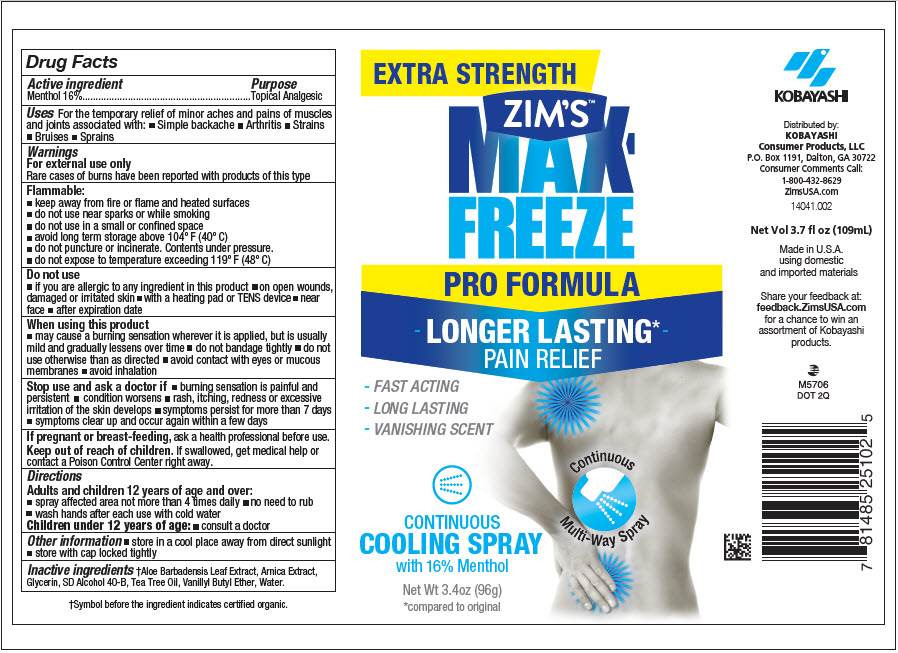 DRUG LABEL: ZIMS MAX FREEZE 
NDC: 54273-008 | Form: SPRAY
Manufacturer: KOBAYASHI Healthcare International, Inc.
Category: otc | Type: HUMAN OTC DRUG LABEL
Date: 20231116

ACTIVE INGREDIENTS: MENTHOL, UNSPECIFIED FORM 160 mg/1 g
INACTIVE INGREDIENTS: ALOE VERA LEAF; ARNICA MONTANA WHOLE; VANILLYL BUTYL ETHER; TEA TREE OIL; GLYCERIN; ALCOHOL; WATER

ZIM'S™ MAX FREEZE
PRO FORMULA

Drug Facts

Active ingredient

Menthol 16%

Purpose

Topical Analgesic

Uses

For the temporary relief of minor aches and pains of muscles and joints associated with:

- Simple backache
- Arthritis
- Strains
- Bruises
- Sprains

Warnings

For external use only

Rare cases of burns have been reported with products of this type

Flammable

- keep away from fire or flame and heated surfaces
- do not use near sparks or while smoking
- do not use in a small or confined space
- avoid long term storage above 104° F (40° C)
- do not puncture or incinerate. Contents under pressure.
- do not expose to temperature exceeding 119° F (48° C)

Do not use

- if you are allergic to any ingredient in this product
- on open wounds, damaged or irritated skin
- with a heating pad or TENS device
- near face
- after expiration date

When using this product

- may cause a burning sensation wherever it is applied, but is usually mild and gradually lessens over time
- do not bandage tightly
- do not use otherwise than as directed
- avoid contact with eyes or mucous membranes
- avoid inhalation

Stop use and ask a doctor if

- burning sensation is painful and persistent
- condition worsens
- rash, itching, redness or excessive irritation of the skin develops
- symptoms persist for more than 7 days
- symptoms clear up and occur again within a few days

PREGNANCY OR BREAST FEEDING

If pregnant or breast-feeding, ask a health professional before use.

Keep out of reach of children. If swallowed, get medical help or contact a Poison Control Center right away.

Directions

Adults and children 12 years of age and over

- spray affected area not more than 4 times daily
- no need to rub
- wash hands after each use with cold water

Children under 12 years of age

- consult a doctor

Other information

- store in a cool place away from direct sunlight
- store with cap locked tightly

Inactive ingredients

[Symbol before the ingredient indicates certified organic.] Aloe Barbadensis Leaf Extract, Arnica Extract, Glycerin, SD Alcohol 40-B, Tea Tree Oil, Vanillyl Butyl Ether, Water.

QUESTIONS

Consumer Comments Call:
1-800-432-8629

Distributed by:
KOBAYASHI
Consumer Products, LLC
P.O. Box 1191, Dalton, GA 30722

PRINCIPAL DISPLAY PANEL - 96 g Can Label

EXTRA STRENGTH

ZIM'S™
MAX-
FREEZE

PRO FORMULA

- LONGER LASTING* -
PAIN RELIEF

- FAST ACTING
- LONG LASTING
- VANISHING SCENT

CONTINUOUS
COOLING SPRAY
with 16% Menthol

Net Wt 3.4oz (96g)
*compared to original

Continuous
Multi-Way Spray